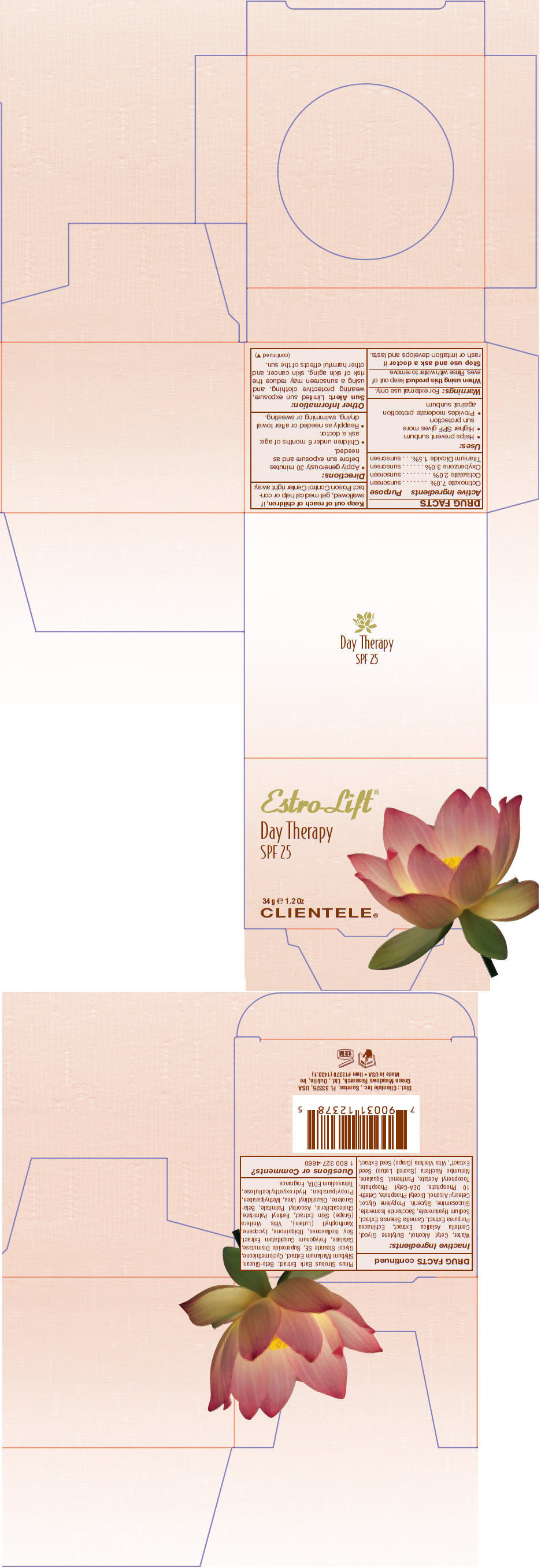 DRUG LABEL: Estro-Lift 
NDC: 64483-003 | Form: CREAM
Manufacturer: Clientele, Inc.
Category: otc | Type: HUMAN OTC DRUG LABEL
Date: 20110901

ACTIVE INGREDIENTS: Octinoxate 7 g/100 g; Octisalate 2 g/100 g; Titanium dioxide 1.5 g/100 g; Oxybenzone 3 g/100 g
INACTIVE INGREDIENTS: Glycerin 1 g/100 g; Alpha-Tocopherol 1 g/100 g; Panthenol 1 g/100 g; Water 54.47 g/100 g; Vitamin A 120000 [iU]/100 g; Cholecalciferol 12000 [iU]/100 g

Estro-Lift®
Day Therapy

ACTIVE INGREDIENT

Active Ingredients | Purpose
Octinoxate 7.0% | sunscreen
Octisalate 2.0% | sunscreen
Oxybenzone 3.0% | sunscreen
Titanium Dioxide 1.5% | sunscreen

Uses

- Helps prevent sunburn
- Higher SPF gives more sun protection
- Provides moderate protection against sunburn

Warnings

For external use only.

When using this product keep out of eyes. Rinse with water to remove.

Stop use and ask a doctor if rash or irritation develops and lasts.

Keep out of reach of children, if swallowed, get medical help or contact Poison Control Center right away.

Directions

- Apply generously 30 minutes before sun exposure and as needed.
- Children under 6 months of age: ask a doctor.
- Reapply as needed or after towel drying, swimming or sweating.

Other Information:

Sun Alert: Limited sun exposure, wearing protective clothing, and using a sunscreen may reduce the risk of skin aging, skin cancer, and other harmful effects of the sun.

Inactive Ingredients

Water, Cetyl Alcohol, Butylene Glycol, Centella Asiatica Extract, Echinacea Purpurea Extract, Camellia Sinensis Extract, Sodium Hyaluronate, Saccharide Isomerate, Glucosamine, Glycerin, Propylene Glycol, Cetearyl Alcohol, Dicetyl Phosphate, Ceteth- 10 Phosphate, DEA-Cetyl Phosphate, Tocopheryl Acetate, Panthenol, Squalane, Nelumbo Nucifera (Sacred Lotus) Seed Extract*, Vitis Vinifera (Grape) Seed Extract, Pinus Strobus Bark Extract, Beta-Glucan, Silybum Marianum Extract, Cyclomethicone, Glycol Stearate SE, Superoxide Dismutase, Catalase, Polygonum Cuspidatum Extract, Soy Isoflavones, Ubiquinone, Lycopene, Xanthophyll (Lutein), Vitis Vinifera (Grape) Skin Extract, Retinyl Palmitate, Cholecalciferol, Ascorbyl Palmitate, Beta- Carotene, Diazolidinyl Urea, Methylparaben, Propylparaben, Hydroxyethylcellulose, Tetrasodium EDTA, Fragrance.

Questions or Comments?

1 800 327-4660

Dist.: Clientele Inc., Sunrise, FL 33325

PRINCIPAL DISPLAY PANEL - 34 g Jar Carton

Estro-Lift®

Day Therapy
SPF 25

34 g e 1.2 Oz
CLIENTELE®